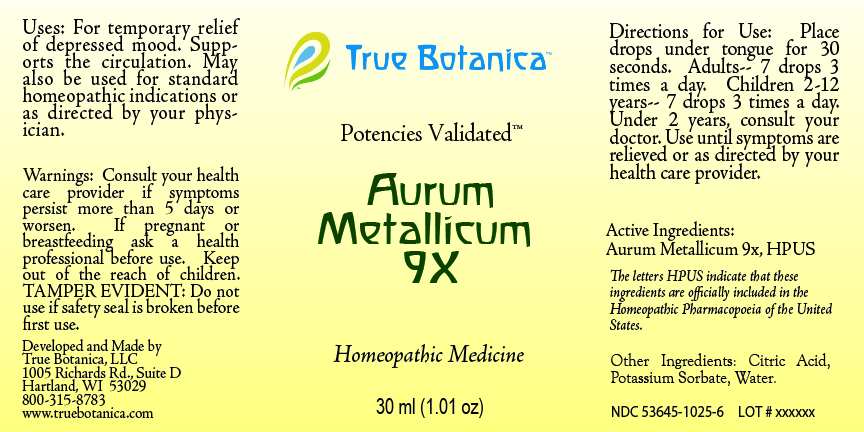 DRUG LABEL: Aurum Metallicum 9X
NDC: 53645-1025 | Form: LIQUID
Manufacturer: True Botanica, LLC
Category: homeopathic | Type: HUMAN OTC DRUG LABEL
Date: 20260219

ACTIVE INGREDIENTS: GOLD 9 [hp_X]/30 mL
INACTIVE INGREDIENTS: POTASSIUM SORBATE; CITRIC ACID MONOHYDRATE; WATER

Aurum Metallicum 9X

ACTIVE INGREDIENT

Aurum Metallicum 9X

PURPOSE

For temporary relief of depressed mood. Supports the circulation. May also be used for standard homeopathic indications or as directed by your physician.

Use:

For temporary relief of depressed mood. Supports the circulation. May also be used for standard homeopathic indications or as directed by your physician.

Warnings:

Consult your health care provider if symptoms persist more than 5 days or worsen.

PREGNANCY OR BREAST FEEDING

If pregnant or breastfeeding ask a health professional before use.

Keep out of the reach of children.

DO NOT USE

TAMPER EVIDENT: Do not use if safety seal is broken before first use.

Directions for Use:

Place drops under tongue for 30 seconds. Adults 7 drops 3 times a day. Children 2-12 years, 7 drops 3 times a day. Under 2 years, consult your doctor. Use until symptoms are relieved or as directed by your health care provider.

Other Ingredients:

Citric Acid, Potassium Sorbate, Water

QUESTIONS

Developed and Made by

True Botanica, LLC

1005 Richards Rd., Suite D

Hartland, WI 53029

800-315-8783

www.truebotanica.com